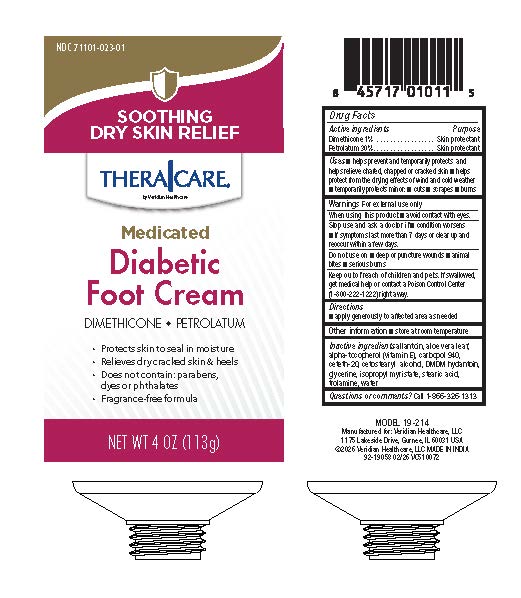 DRUG LABEL: TheraCare Diabetic Foot Cream
NDC: 71101-023 | Form: CREAM
Manufacturer: Veridian Healthcare
Category: otc | Type: HUMAN OTC DRUG LABEL
Date: 20260129

ACTIVE INGREDIENTS: PETROLATUM 30 g/100 g; DIMETHICONE 1 g/100 g
INACTIVE INGREDIENTS: CARBOMER 940; GLYCERIN; CETOSTEARYL ALCOHOL; ISOPROPYL MYRISTATE; CETETH-20; STEARIC ACID; DMDM HYDANTOIN; ALOE VERA LEAF; .ALPHA.-TOCOPHEROL; ALLANTOIN; TROLAMINE; WATER

TheraCare Diabetic Foot Cream

Active Ingredient

Dimethicone 1%..............................Skin Protectant

Petrolatum 30%..............................Skin Protectant

Purpose

Skin Protectant

Uses

■helps relieve, prevent and, temporarily protects chafed, chapped or cracked skin

■helps protect from the drying effects of wind and cold weather

■ temporarily protects minor cuts, scrapes, and burns

Warnings

For external use only.

When using this product

avoid contact with eyes.

Stop use and ask physician if

- condition worsens
- if symptoms last more than 7 days or clear up and occur again within a few days

Do not use on

- deep or puncture wounds
- animal bites
- serious burns

Keep out of reach of children

If swallowed, get medical help or contact a Poison Control Center (1-800-222-1222) right away.

Directions

Apply generously to affected area as needed.

Other information

Store at room temperature

Inactive Ingredients

allantoin, aloe vera leaf, alpha-tocopherol (vitamin E), carbopol 940, ceteth-20, cetostearyl alcohol, DMDM hydantoin, glycerine, isopropyl myristate, stearic acid, trolamine, water

Questions?

Call 1-866-326-1313